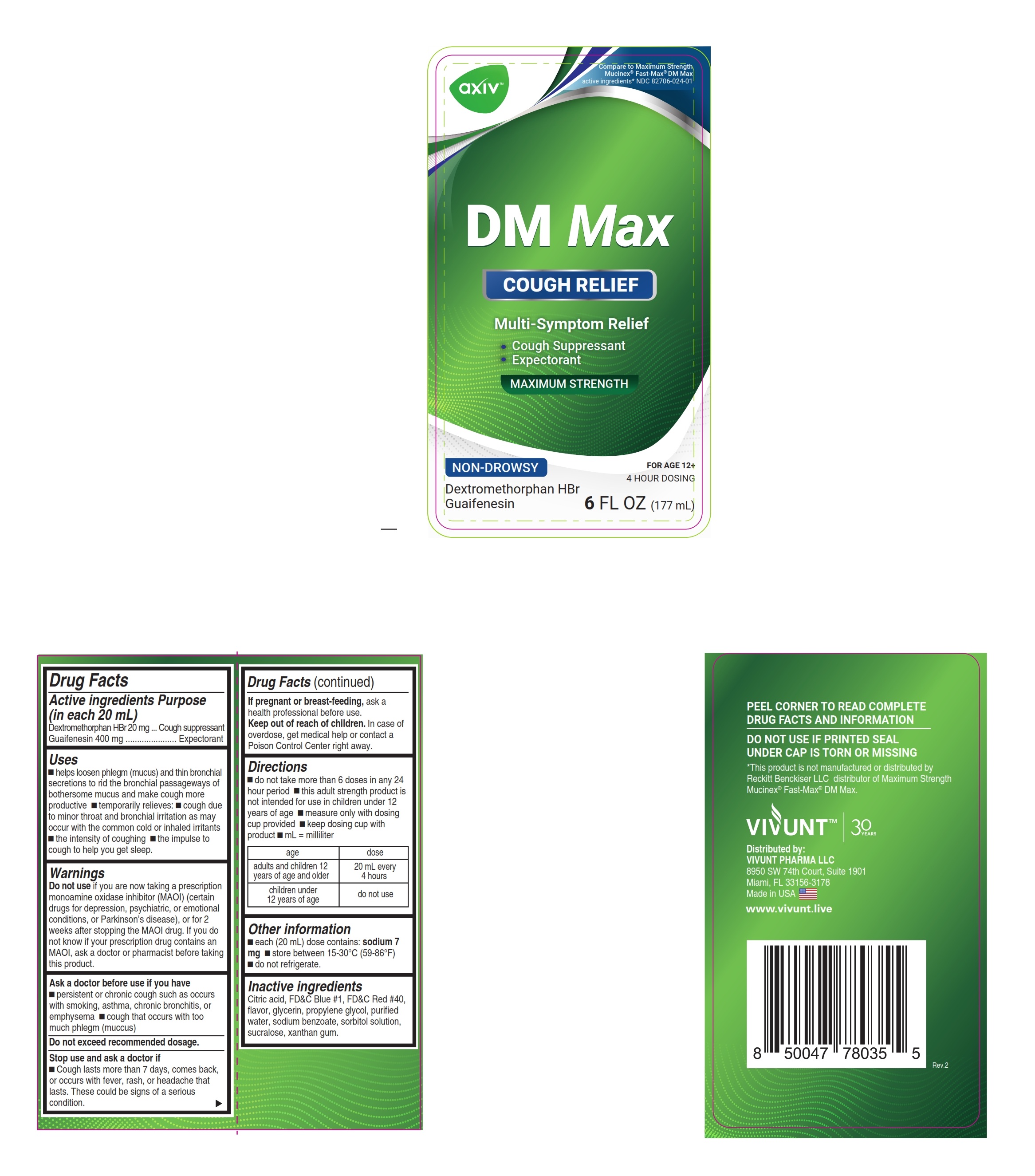 DRUG LABEL: AXIV DM Max
NDC: 82706-024 | Form: LIQUID
Manufacturer: VIVUNT PHARMA LLC
Category: otc | Type: HUMAN OTC DRUG LABEL
Date: 20240514

ACTIVE INGREDIENTS: DEXTROMETHORPHAN HYDROBROMIDE 20 mg/20 mL; GUAIFENESIN 400 mg/20 mL
INACTIVE INGREDIENTS: PROPYLENE GLYCOL; CITRIC ACID MONOHYDRATE; FD&C RED NO. 40; SODIUM BENZOATE; SORBITOL SOLUTION; SUCRALOSE; XANTHAN GUM; WATER; GLYCERIN; FD&C BLUE NO. 1

AXIV DM MAX - Liquid

Drug Facts

ACTIVE INGREDIENT

PURPOSE

Active ingredients (in each 20 mL) | Purposes
Dextromethorphan HBr 20 mg | Cough suppressant
Guaifenesin 400 mg | Expectorant

Uses

- helps loosen phlegm (mucus) and thin bronchial secretions to rid the bronchial passageways of bothersome mucus and make coughs more productive
- temporarily relieves:
  - cough due to minor throat and bronchial irritation as may occur with the common cold or inhaled irritants
  - the intensity of coughing
  - the impulse to cough to help you get to sleep

Warnings

Do not use

- if you are now taking a prescription monoamine oxidase inhibitor (MAOI) (certain drugs for depression, psychiatric, or emotional conditions, or Parkinson's disease), or for 2 weeks after stopping the MAOI drug. If you do not know if your prescription drug contains an MAOI, ask a doctor or pharmacist before taking this product.

Ask a doctor before use if you have

- persistent or chronic cough such as occurs with smoking, asthma, chronic bronchitis, or emphysema
- cough that occurs with too much phlegm (mucus)

WHEN USING

Do not exceed recommended dosage.

Stop use and ask a doctor if

- cough lasts more than 7 days, comes back, or occurs with fever, rash, or headache that lasts. These could be signs of a serious condition.

If pregnant or breast-feeding,

ask a health professional before use.

Keep out of reach of children.

In case of overdose, get medical help or contact a Poison Control Center right away.

Directions

- do not take more than 6 doses in any 24-hour period
- this adult strength product is not intended for use in children under 12 years of age
- measure only with dosing cup provided
- keep dosing cup with product
- mL = milliliter

age | dose
adults and children 12 years of age and older | 20 mL every 4 hours
children under 12 years of age | do not use

Other information

- each 20 mL contains: sodium 7 mg
- store at 15-30°C (59-86°F)
- do not refrigerate

Inactive ingredients

Citric acid, FD&C Blue #1, FD&C red no. 40, flavor, glycerin, propylene glycol, purified water, sodium benzoate, sorbitol solution, sucralose, xanthan gum.

PEEL CORNER TO READ COMPLETE DRUG FACTS AND INFORMATION/ DO NOT USE IF PRINTED SEAL UNDER CAP IS TORN OR MISSING

Distributed by:

VIVUNT PHARMA LLC

8950 SW 74th Court, Suite 1901

Miami, FL 33156-3178

Made in USA

www.vivunt.live

PRINCIPAL DISPLAY PANEL

Compare to Maximum Strength Mucinex® Fast-Max®

NDC 82706-024-01

AXIV - DM MAX

Cough Relief

Cough Suppressant
Expectorant

Maximum Strength

Non-Drowsy

Dextromethorphan HBr

Guaifenesin

6 FL OZ (177 mL)